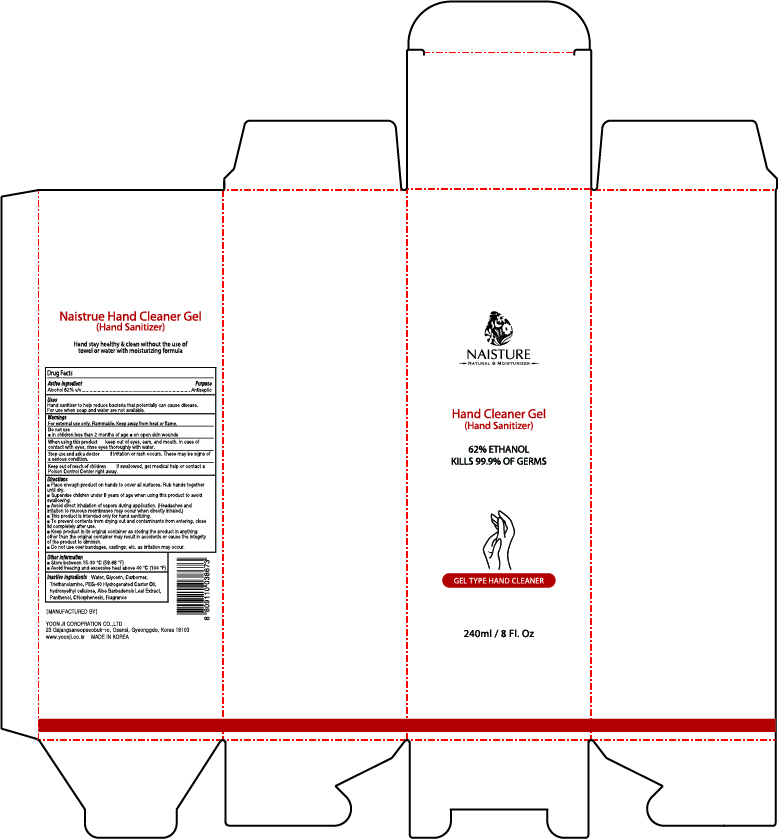 DRUG LABEL: Naisture Hand Cleaner Gel(Hand Sanitizer)
NDC: 75024-240 | Form: GEL
Manufacturer: YOON JI CORPORATION CO.,LTD
Category: otc | Type: HUMAN OTC DRUG LABEL
Date: 20200416

ACTIVE INGREDIENTS: ALCOHOL 148.8 mL/240 mL
INACTIVE INGREDIENTS: CHLORPHENESIN; HYDROXYETHYL CELLULOSE, UNSPECIFIED; ALOE VERA LEAF; GLYCERIN; TROLAMINE; CARBOMER HOMOPOLYMER, UNSPECIFIED TYPE; WATER; PANTHENOL; POLYOXYL 40 HYDROGENATED CASTOR OIL

Naisture Hand Sanitizer 240 ml : 75024-240-02